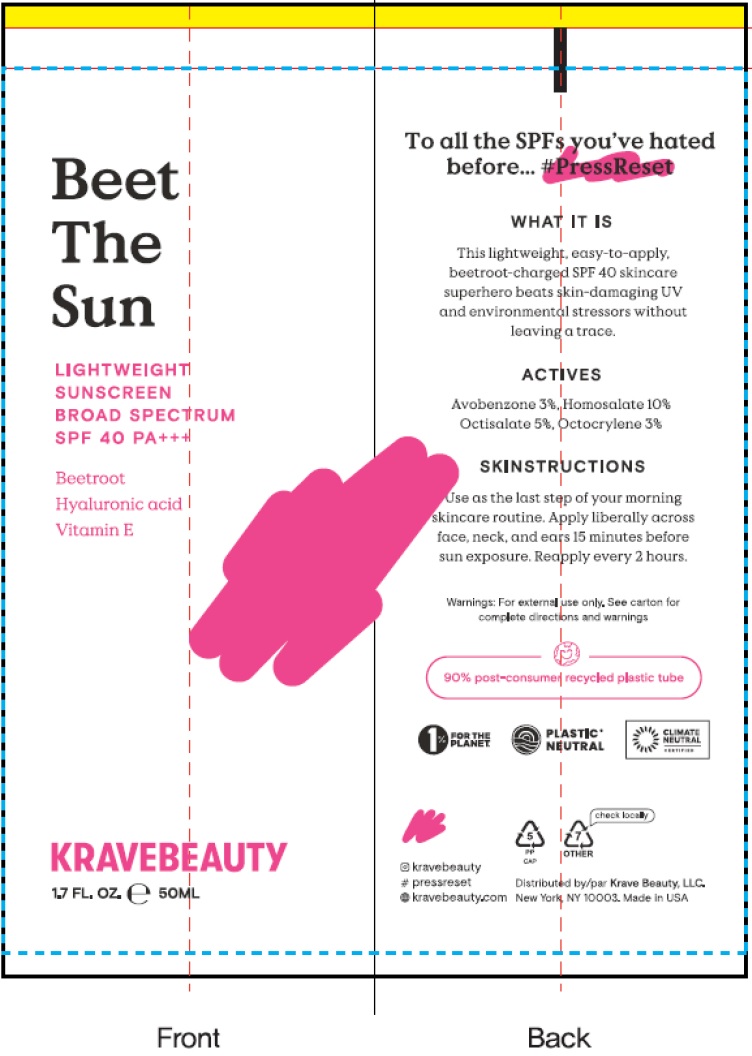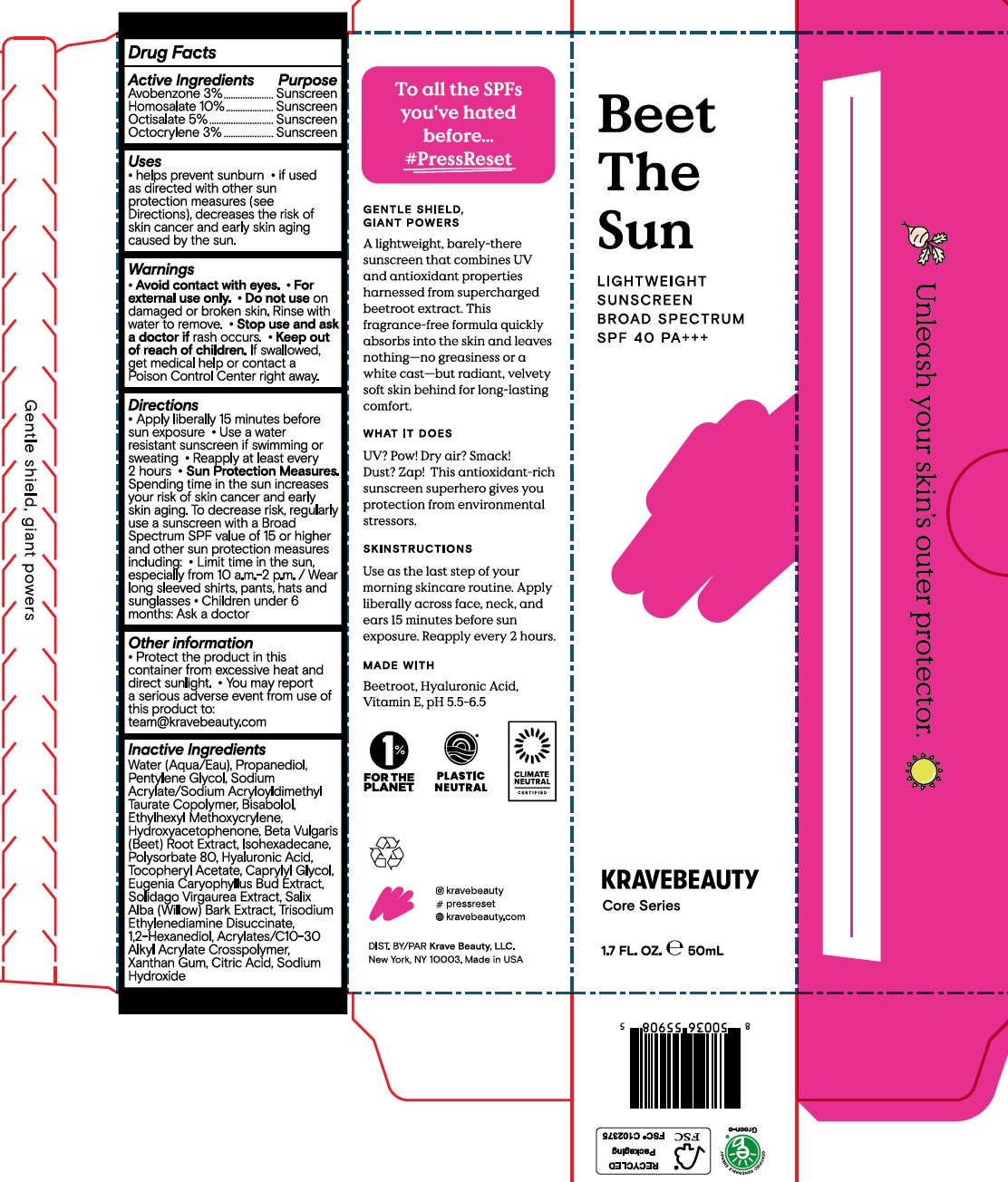 DRUG LABEL: Beet the sun lightweight sunscreen broad spectrum spf 40 pa
NDC: 83493-150 | Form: LOTION
Manufacturer: Krave Beauty, LLC
Category: otc | Type: HUMAN OTC DRUG LABEL
Date: 20231212

ACTIVE INGREDIENTS: AVOBENZONE 30 mg/1 mL; HOMOSALATE 100 mg/1 mL; OCTISALATE 50 mg/1 mL; OCTOCRYLENE 30 mg/1 mL
INACTIVE INGREDIENTS: WATER; PROPANEDIOL; PENTYLENE GLYCOL; LEVOMENOL; ETHYLHEXYL METHOXYCRYLENE; HYDROXYACETOPHENONE; BEET; ISOHEXADECANE; POLYSORBATE 80; HYALURONIC ACID; .ALPHA.-TOCOPHEROL ACETATE; CAPRYLYL GLYCOL; SALIX ALBA BARK; TRISODIUM ETHYLENEDIAMINE DISUCCINATE; 1,2-HEXANEDIOL; XANTHAN GUM; CITRIC ACID MONOHYDRATE; SODIUM HYDROXIDE

Beet the sun lightweight sunscreen broad spectrum spf 40 pa+++

Active Ingredients

Avobenzone 3%

Homosalate 10%

Octisalate 5%

Octocrylene 3%

Purpose

Sunscreen

Uses

- helps prevent sunburn
- if used as directed with other sun protection measures (see Directions), decreases the risk of skin cancer and early skin aging caused by the sun.

Warnings

- Avoid contact with eyes.
- For external use only.

Do not use

- on damaged or broken skin. Rinse with water to remove.

Stop use and ask a doctor if

- rash occurs.

Keep out of reach of children.

- If swallowed, get medical help or contact a Poison Control Center right away.

Directions

- Apply liberally 15 minutes before sun exposure
- Use a water resistant sunscreen if swimming or sweating
- Reapply at least every 2 hours
- Spending time in the sun increases your risk of skin cancer and early skin aging. To decrease risk, regularly use a sunscreen SPF value of 15 or higher and other sun protection measures including: Sun Protection Measures.
- limit time in the sun, especially from 10 a.m.-2 p.m. / Wear long sleeved shirts, pants, hats and sunglasses
- Children under 6 months: Ask a doctor

Other information

- Protect the product in this container from excessive heat and direct sunlight.
- You may report a serious adverse event from use of this product to: team@kravebeauty.com

Inactive Ingredients

Water (Aqua), Propanediol, Pentylene Glycol, Sodium Acrylate/Sodium Acryloyldimethyl Taurate Copolymer, Bisabolol, Ethylhexyl Methoxycrylene, Hydroxyacetophenone, Beta Vulgaris (Beet) Root Extract, Isohexadecane, Polysorbate 80, Hyaluronic Acid, Tocopheryl Acetate, Caprylyl Glycol, Eugenia Caryophyllus Bud Extract, Solidago Virgaurea Extract, Salix Alba (Willow) Bark Extract, Trisodium Ethylenediamine Disuccinate, 1,2-Hexanediol, Acrylates/C10-30 Alkyl Acrylate Crosspolymer, Xanthan Gum, Citric Acid, Sodium Hydroxide